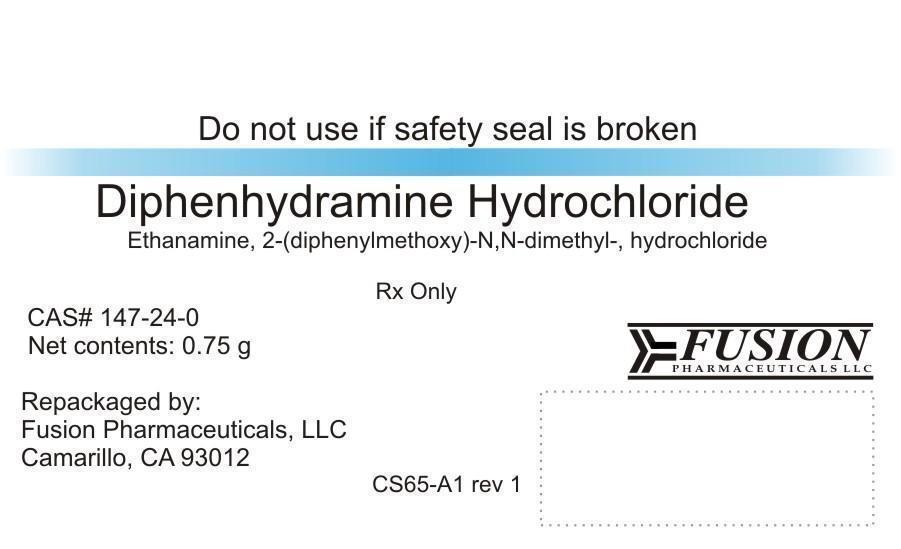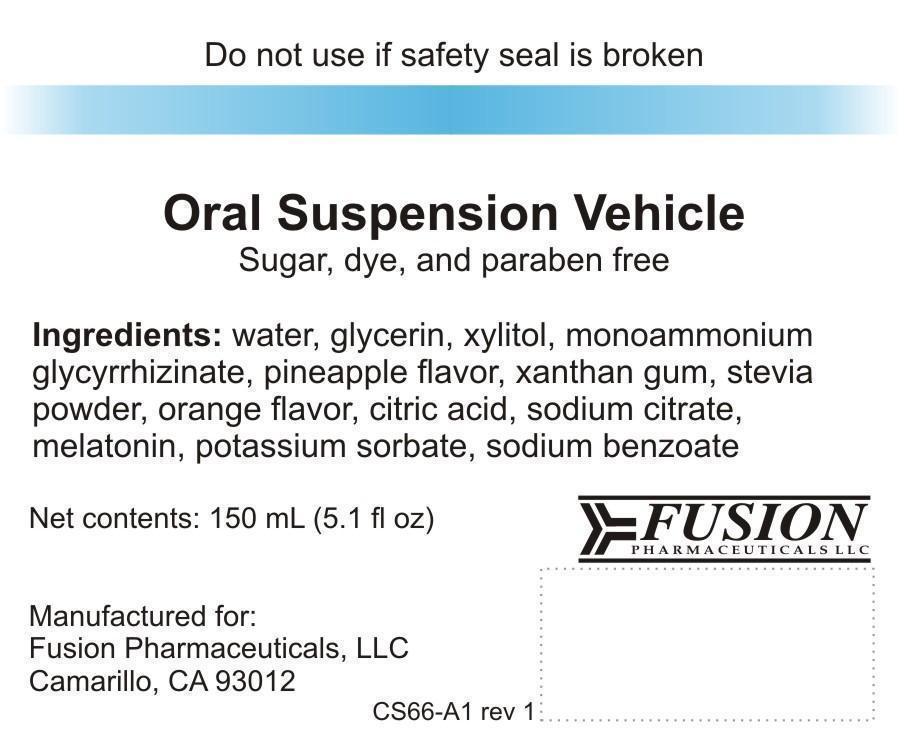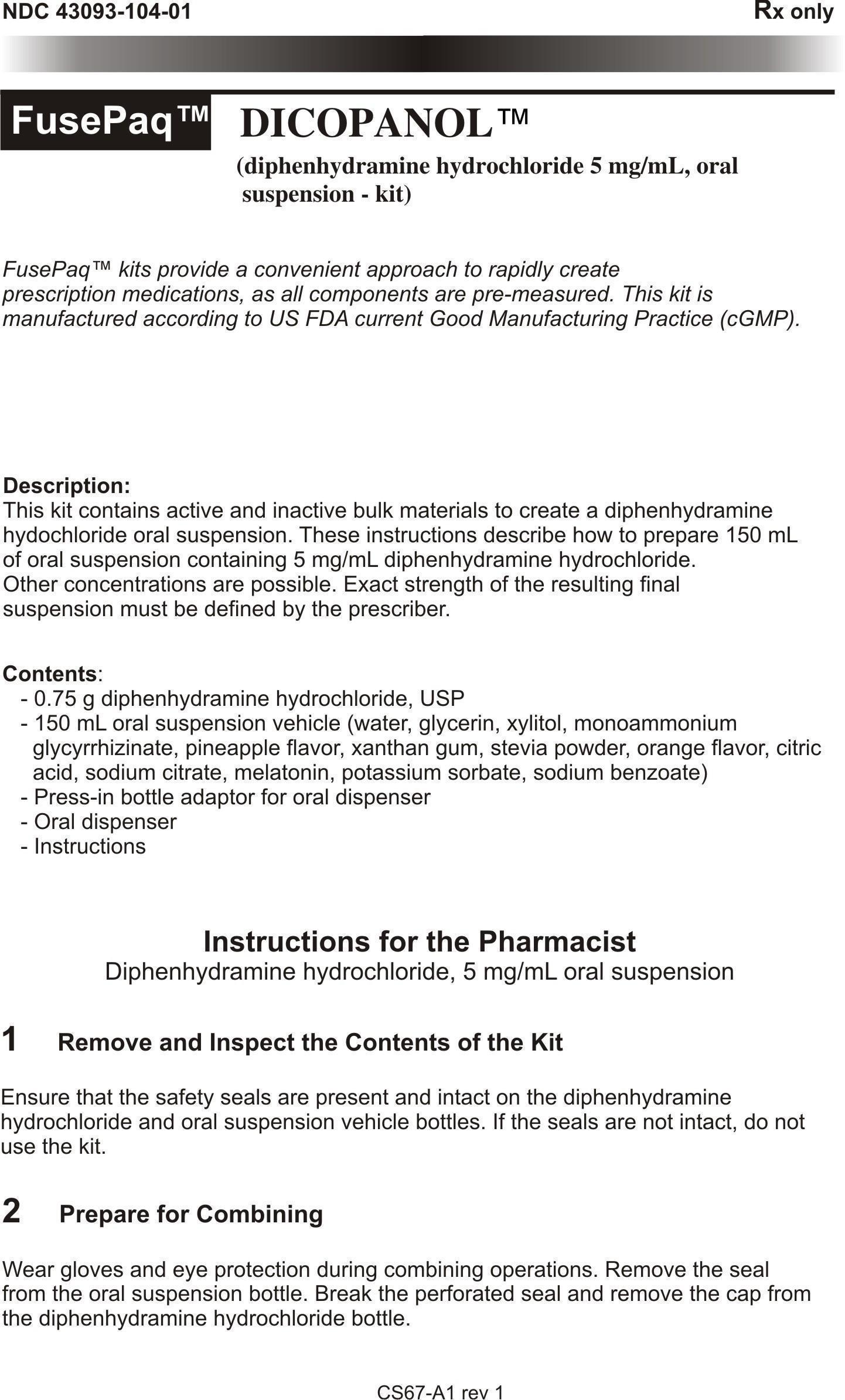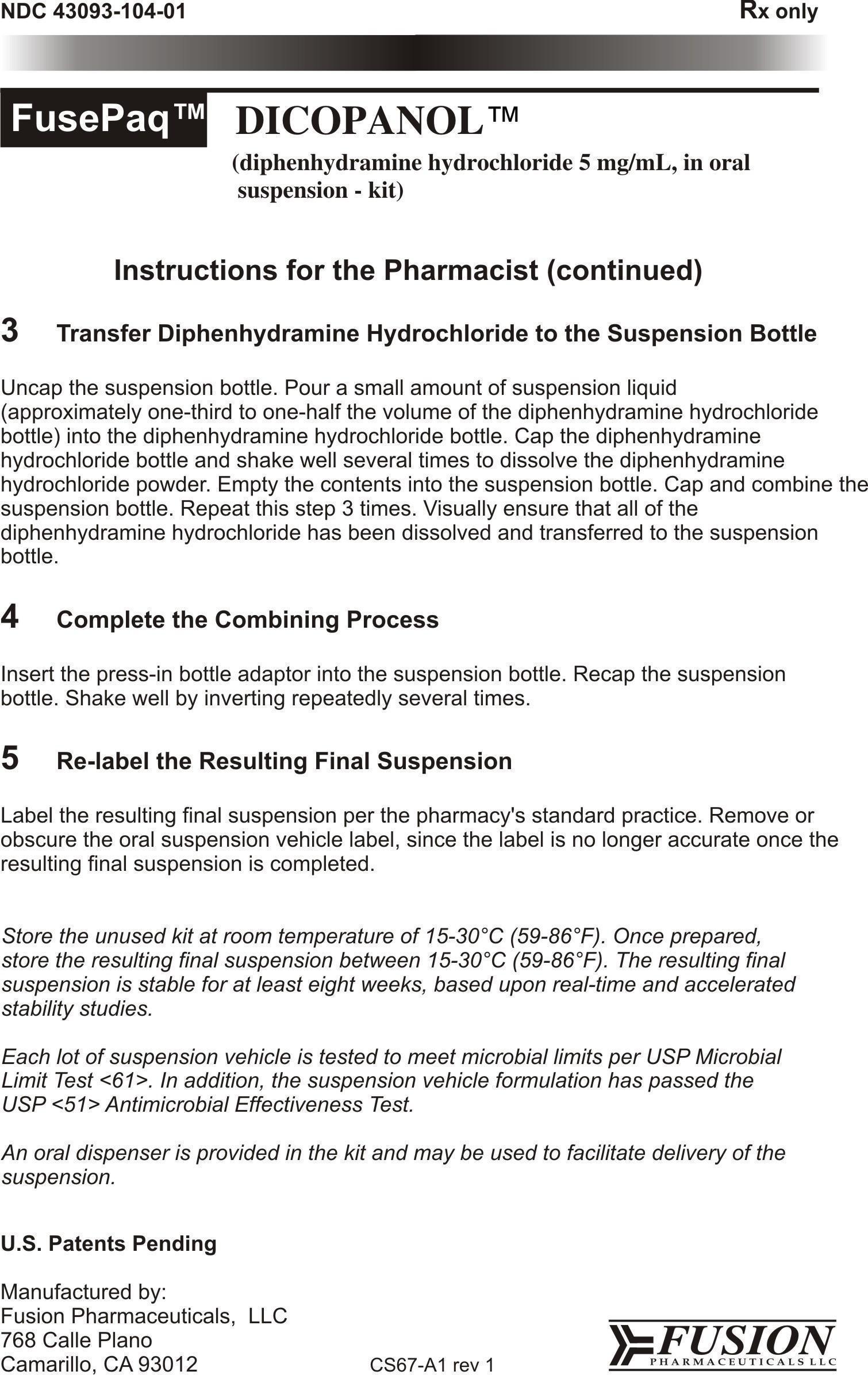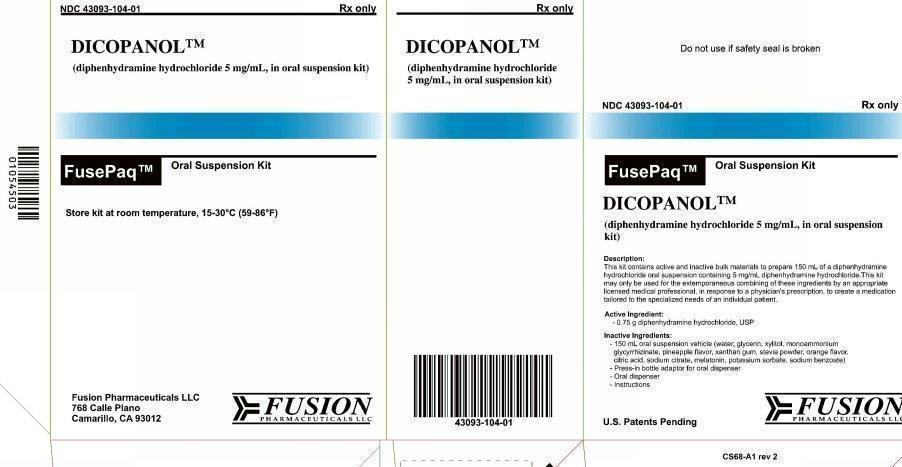 DRUG LABEL: Dicopanol
NDC: 43093-104 | Form: KIT | Route: ORAL
Manufacturer: Fusion Pharmaceuticals LLC
Category: prescription | Type: HUMAN PRESCRIPTION DRUG LABEL
Date: 20151119

ACTIVE INGREDIENTS: DIPHENHYDRAMINE HYDROCHLORIDE 0.75 g/0.75 g
INACTIVE INGREDIENTS: WATER; GLYCERIN; XYLITOL; GLYCYRRHIZIN, AMMONIATED; PINEAPPLE; XANTHAN GUM; STEVIA LEAF; ORANGE; CITRIC ACID MONOHYDRATE; SODIUM CITRATE; MELATONIN; POTASSIUM SORBATE; SODIUM BENZOATE

DICOPANOL

Principal Display Panel

Do not use if safety seal is broken
NDC 43093-104-01
Rx only
FusePaq™ Oral Suspension Kit
DICOPANOL™
(diphenhydramine hydrochloride 5 mg/mL, in oral suspension kit)
Description:
This kit contains active and inactive bulk materials to prepare 150 mL of a diphenhydramine hydrochloride oral suspension containing 5 mg/mL diphenhydramine hydrochloride. This kit may only be used for the extemporaneous combining of these ingredients by an appropriate licensed medical professional in response to a physician's prescription to create a medication tailored to the specialized needs of an individual patient.
Active Ingredient:

- 0.75 g diphenhydramine hydrochloride, USP

Inactive Ingredients:

- 150 mL oral suspension vehicle (water, glycerin, xylitol, monoammonium glycyrrhizinate, pineapple flavor, xanthan gum, stevia powder, orange flavor, citric acid, sodium citrate, melatonin, potassium sorbate, sodium benzoate)
- Press-in bottle adaptor for oral dispenser
- Oral dispenser
- Instructions

Store kit at room temperature, 15-30 degrees C (59-86 degrees F)
U.S. Patents Pending FUSION PHARMACEUTICALS 786 Calle Plano Camarillo CA 93012
CS68-A1 rev 2

Drug Label

Do not use if safety seal is broken

Diphenhydramine Hydrochloride
Ethanamine, 2-(diphenylmethoxy)-N,N-dimethyl-, hydrochloride
Rx Only
CAS# 147-24-0
Net contents: 0.75 g
Repackaged by:
Fusion Pharmaceuticals, LLC
Camarillo, CA 93012
CS65-A1 rev 1

Suspension Label

Do not use if safety seal is broken
Oral Suspension Vehicle
Sugar, dye, and paraben free
Ingredients: water, glycerin, xylitol, monoammonium glycyrrhizinate, pineapple flavor, xanthan gum, stevia powder, orange flavor, citric acid, sodium citrate, melatonin, potassium sorbate, sodium benzoate
Net Contents: 150 mL (5.1 fl oz)
Manufactured for:
Fusion Pharmaceuticals, LLC
Camarillo, CA 93012
CS66-A1 rev 1

Instructions Insert

NDC 43093-104-01
Rx Only
FusePaq tm DICOPANOL tm
(diphenhydramine hydrochloride 5 mg/mL, oral suspension- kit)
FusePaq tm kits provide a convenient approach to rapidly create prescription medications, as all components are pre-measured. This kit is manufactures according to US FDA current Good Manufacturing Practice (cGMP).
Description:
This kit contains active and inactive bulk materials to create a diphenhydramine hydrochloride oral suspension. These instructions describe how to prepare 150 mL of oral suspension containing 5 mg/mL diphenhydramine hydrochloride. Other concentrations are possible. Exact strength of the resulting final suspension must be defined by the prescriber.
Contents:
- 0.75 g diphenhydramine hydrochloride, USP
- 150 mL oral suspension vehicle (water, glycerin, xylitol, monoammonium glycyrrhizinate, pineapple flavor, xanthan gum, stevia powder, orange flavor, citric acid, sodium citrate, melatonin, potassium sorbate, sodium benzoate)
Instructions for the Pharmacist
Diphenhydramine hydrochloride, 5 mg/mL oral suspension
1 Remove and Inspect the Contents of the Kit
Ensure that the safety seals are present and intact on the diphenhydramine hydrochloride and oral suspension vehicle bottles. If the seals are not intact, do not use the kit.
2 Prepare for Combining
Wear gloves and eye protection during combining operations. Remove the seal from the oral suspension bottle. Break the perforated seal and remove the cap from the diphenhydramine hydrochloride bottle.
3 Transfer Diphenhydramine Hydrochloride to the Suspension Bottle
Uncap the suspension bottle. Pour a small amount of suspension liquid (approximately one-third to one-half the volume of the diphenhydramine hydrochloride bottle) into the diphenhydramine hydrochloride bottle. Cap the diphenhydramine hydrochloride bottle and shake well several times to dissolve the diphenhydramine hydrochloride powder. Empty the contents into the suspension bottle. Cap and combine the suspension bottle. Repeat this step 3 times. Visually ensure that all of the diphenhydramine hydrochloride has been dissolved and transferred to the suspension bottle.
4 Complete the Combining Process
Insert the press-in bottle adaptor into the suspension bottle. Recap the suspension bottle. Shake well by inverting repeatedly several times.
5 Re-label the Resulting Final Suspension
Label the resulting final suspension per the pharmacy's standard practice. Remove or obscure the oral suspension vehicle label, since the label is no longer accurate once the resulting final suspension is completed.
Store the unused kit at room temperature of 15-30°C (59-86°F). Once prepared, store the resulting final suspension between 15-30°C (59-86°F). The resulting final suspension is stable for at least eight weeks, based upon real-time and accelerated stability studies.
Each lot of suspension vehicle is tested to meet microbial limits per USP Microbial Limit Test 61. In addition, the suspension vehicle formulation has passed the USP 51 Antimicrobial Effectiveness Test.
An oral dispenser is provided in the kit and may be used to facilitate delivery of the suspension.
U.S. Patents Pending
Manufactured by:
Fusion Pharmaceuticals, LLC
768 Calle Plano
Camarillo, CA 93012
CS67-A1 rev 1